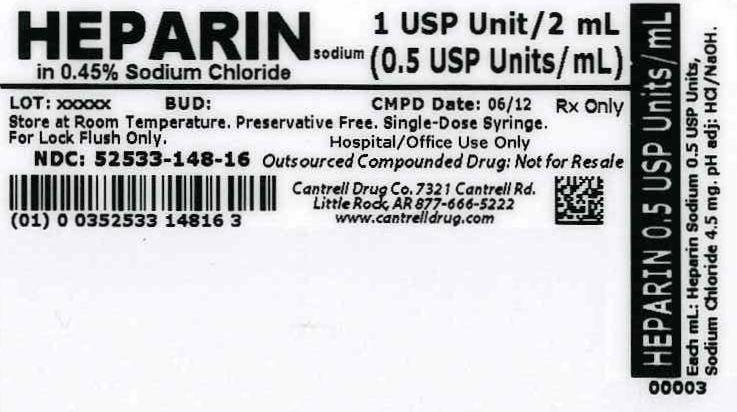 DRUG LABEL: Heparin Sodium
NDC: 52533-148 | Form: INJECTION, SOLUTION
Manufacturer: Cantrell Drug Company
Category: prescription | Type: HUMAN PRESCRIPTION DRUG LABEL
Date: 20140501

ACTIVE INGREDIENTS: Heparin Sodium 0.5 [USP'U]/1 mL
INACTIVE INGREDIENTS: Sodium Chloride 4.5 mg/1 mL; WATER

Heparin Sodium 0.5 USP Units/mL in 0.45% Sodium Chloride 2 mL Syringe